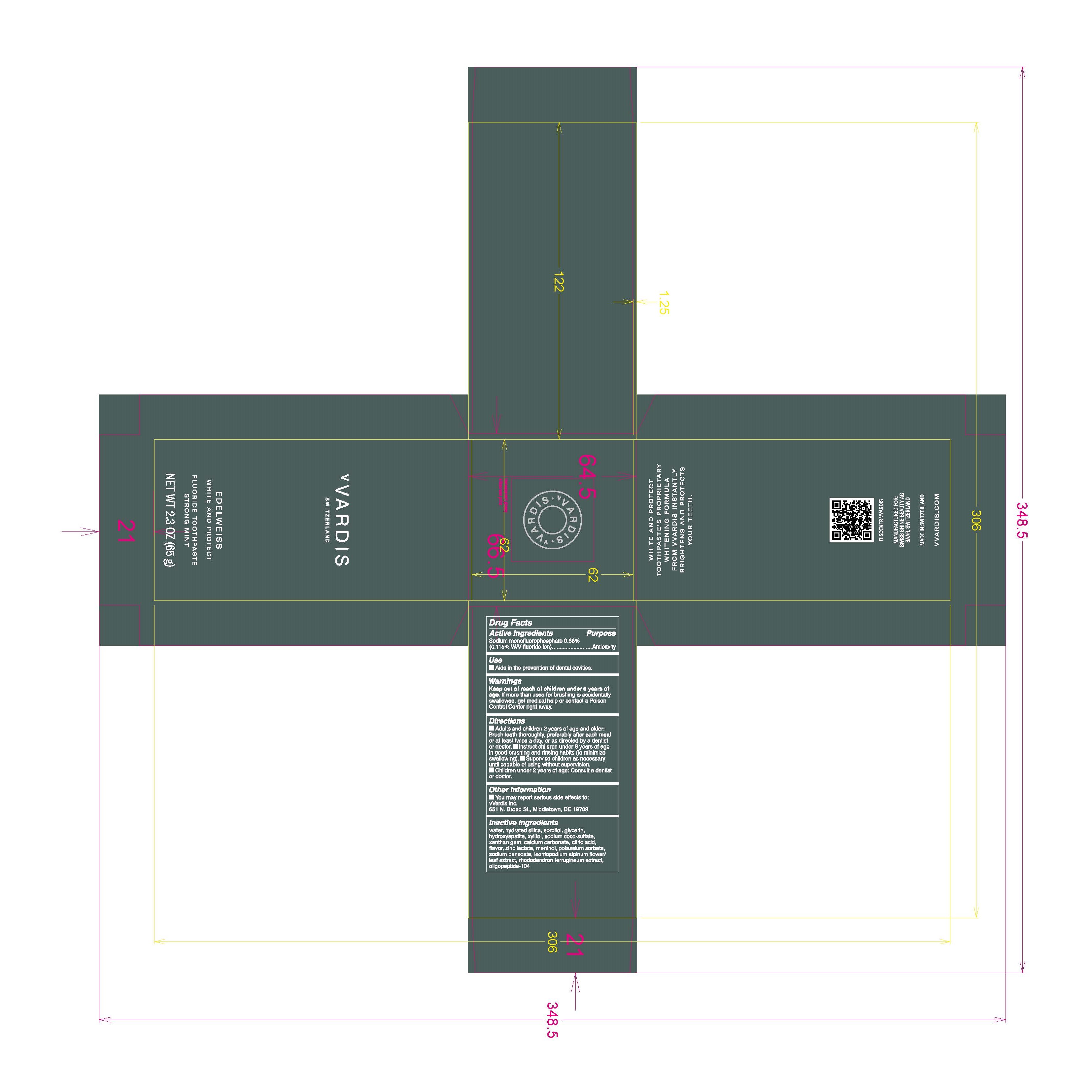 DRUG LABEL: Fluoride Strong Mint
NDC: 79763-007 | Form: PASTE
Manufacturer: Swiss Shine Beauty AG
Category: otc | Type: HUMAN OTC DRUG LABEL
Date: 20220120

ACTIVE INGREDIENTS: SODIUM MONOFLUOROPHOSPHATE 0.88 g/100 g
INACTIVE INGREDIENTS: ZINC LACTATE; HYDRATED SILICA; SORBITOL; GLYCERIN; SODIUM COCO-SULFATE; POTASSIUM SORBATE; XANTHAN GUM; WATER; CITRIC ACID MONOHYDRATE; CALCIUM CARBONATE; XYLITOL; MENTHOL, UNSPECIFIED FORM; LEONTOPODIUM NIVALE SUBSP. ALPINUM FLOWERING TOP; SODIUM BENZOATE; RHODODENDRON FERRUGINEUM WHOLE; TRIBASIC CALCIUM PHOSPHATE

Fluoride Strong Mint

Active Ingredients Purpose

sodium monofluorophosphate 0.88% Anticavity

(0.115% W/V fluoride)

Use

- Aids in the prevention of dental cavities

Keep out of reach of children under 6 years of age.

INDICATIONS AND USAGE

If more than used for brushing is accidentally swallowed, get medical help or contact a poison control center right away.

Keep out of reach of children under 6 years of age.If more than used for brushing is accidentally swallowed, get medical help or contact a Poison Control Center right away.

Directions

- Adults and children 2 years of age and older:Brush teeth thoroughly, preferable after each meal or at least twice a day, or as directed by a dentist or doctor.
- Instruct children under 6 years of age in good brushing and rinsing habits (to minimize swallowing)
- Supervise children as necessary until capable of using without supervision
- Children under 2 years of age: consult a dentist or doctor

Inactive Ingredients

water, hydrated silica, sorbitol, glycerin, hydroxyapatite, xylitol, sodium coco-sulfate, xanthan gum, calcium carbonate, citric acid, flavor, zinc lactate, menthol, potassium sorbate, sodium benzoate, leontopodium alpinum flower/leaf extract, rhododendron ferrugineum extract, oligopeptide-104

PACKAGE LABEL

vVardis Switzerland

edelwiess

white and protect

Fluoride Toothpaste Strong Mint

NET WT 2.3 OZ (65 g)